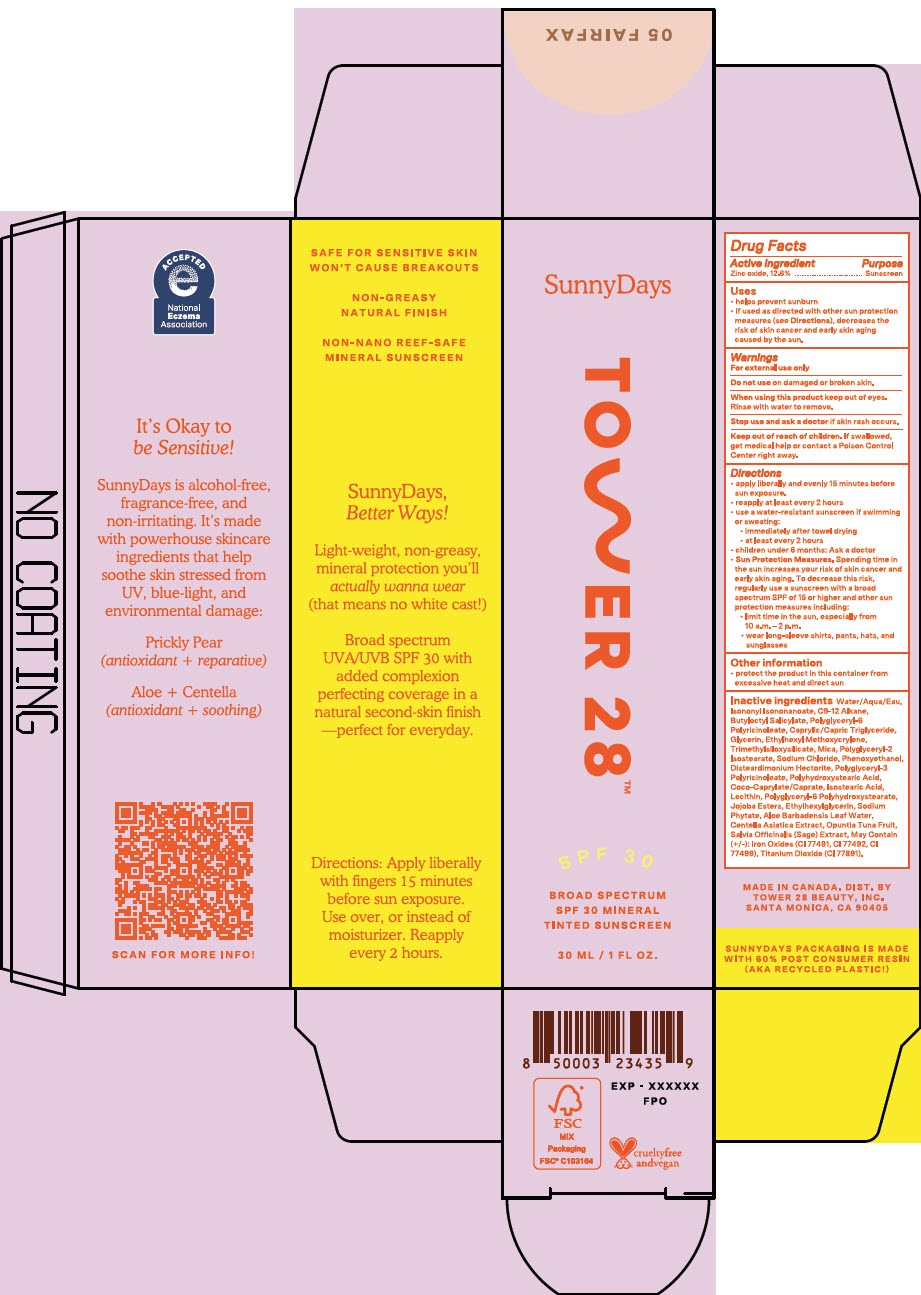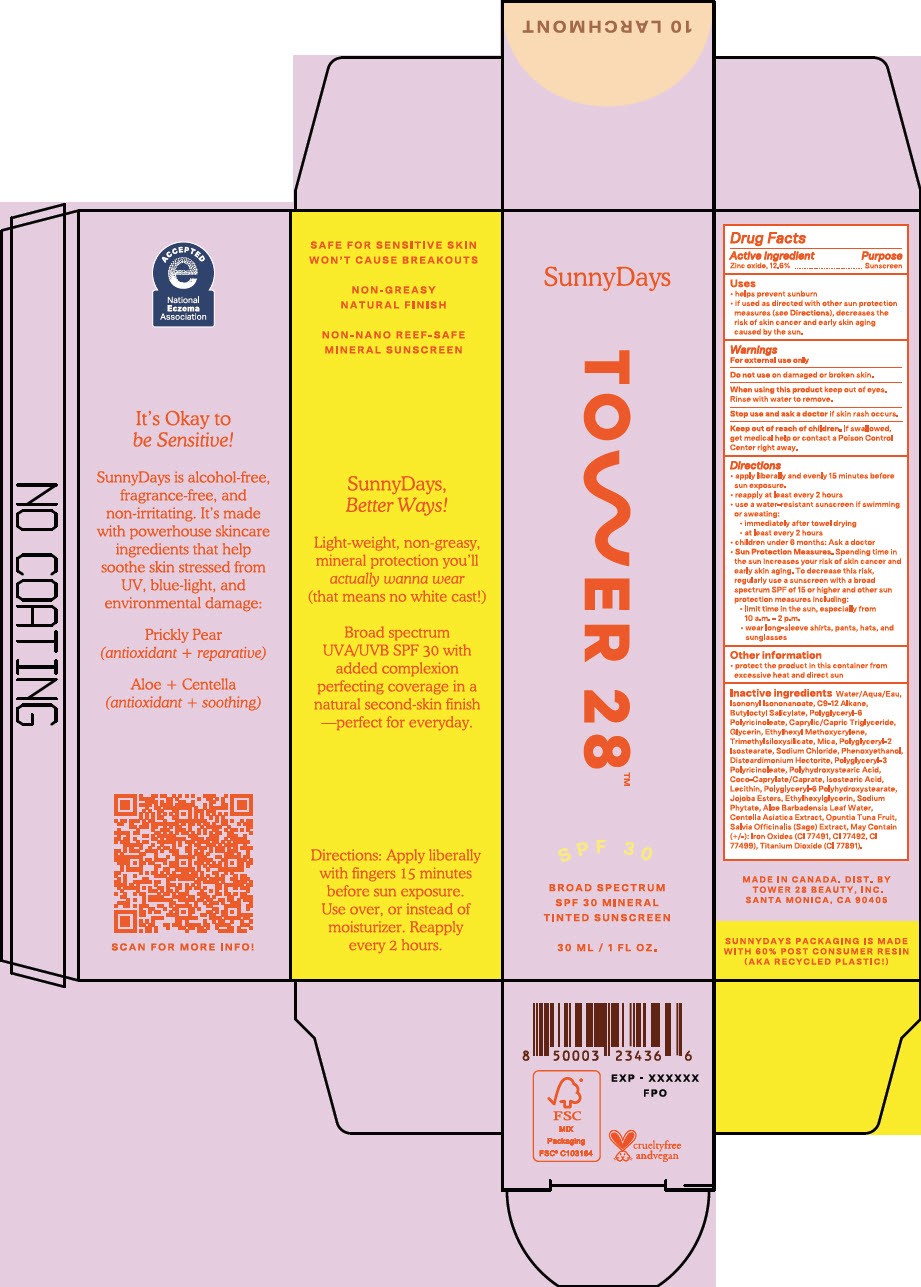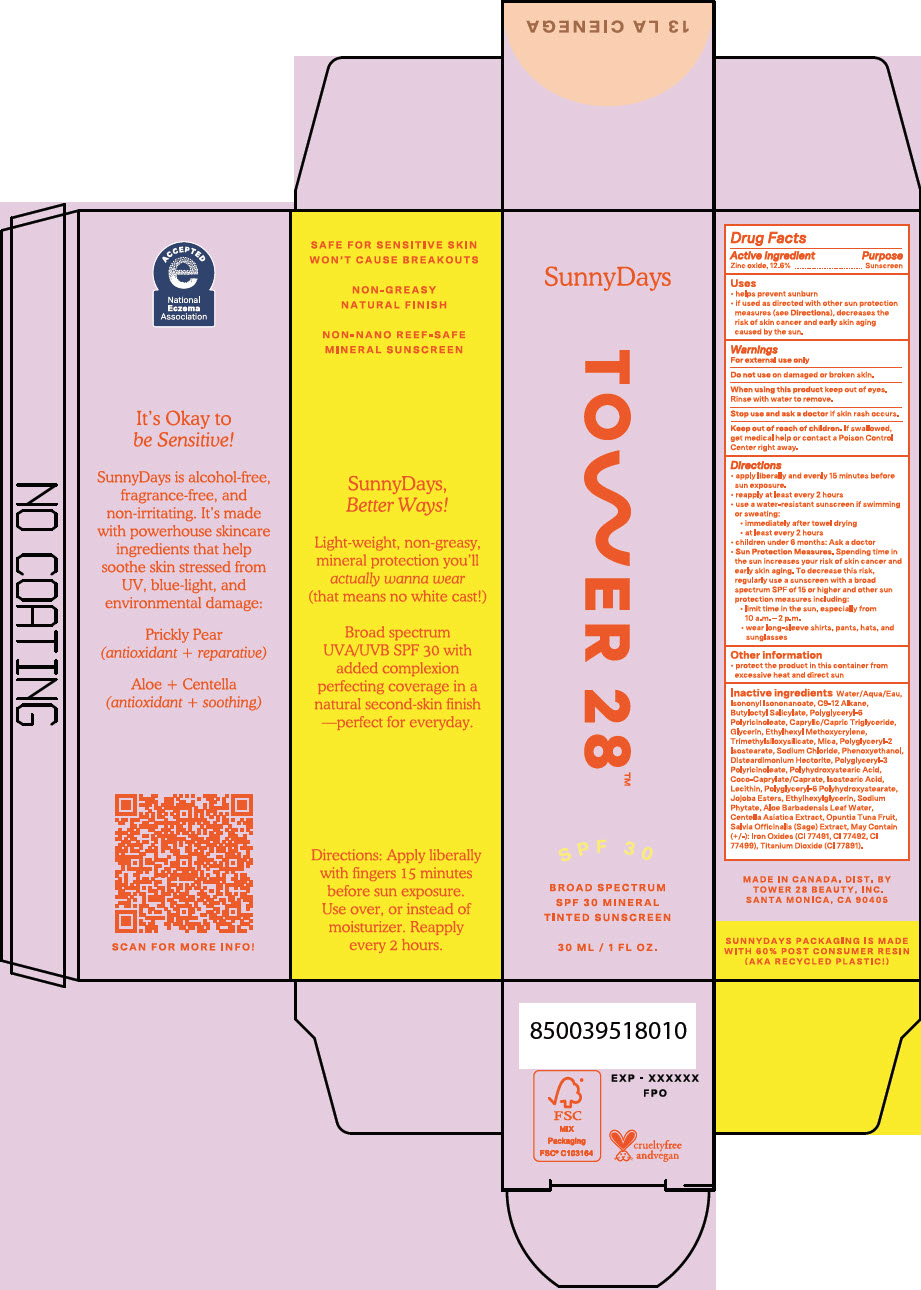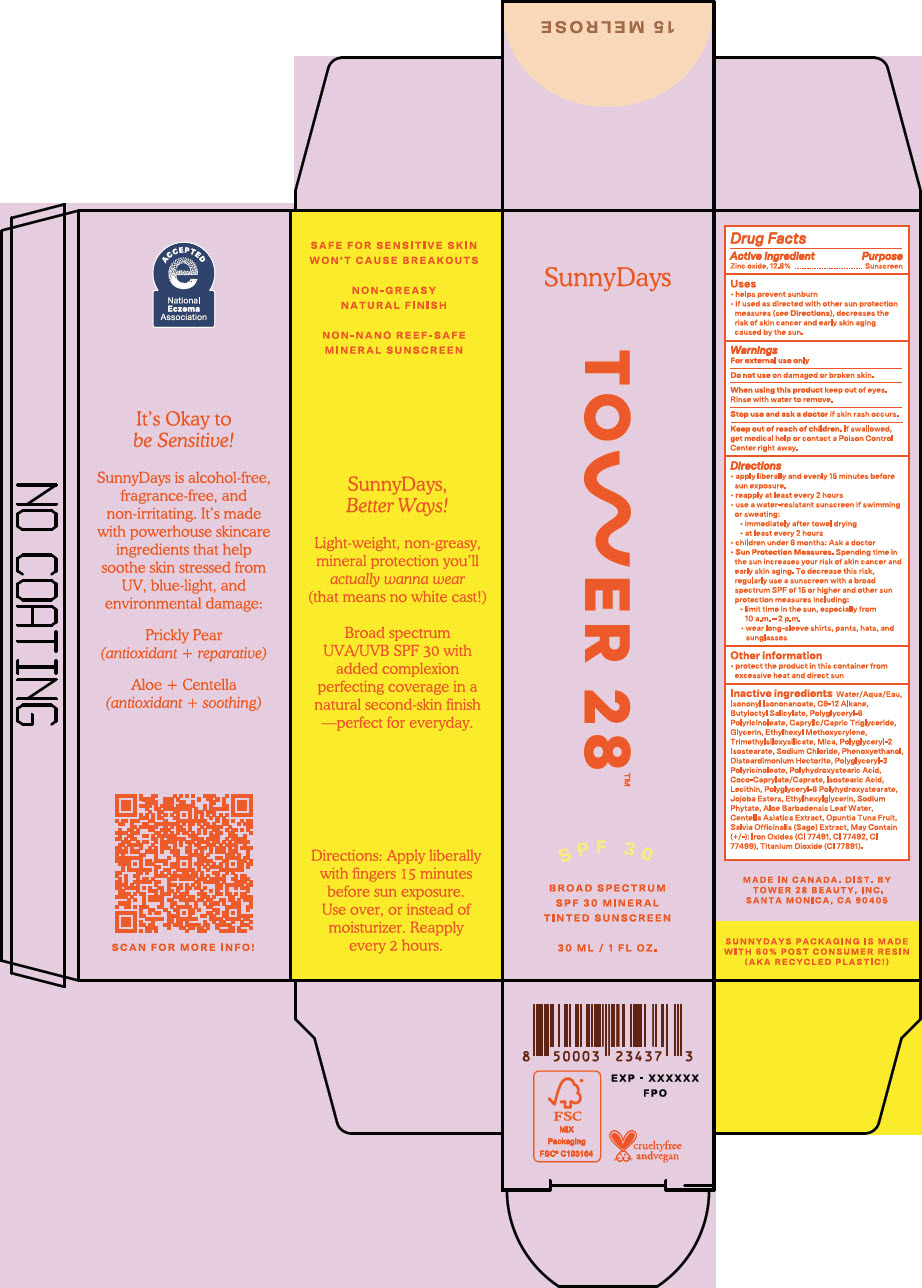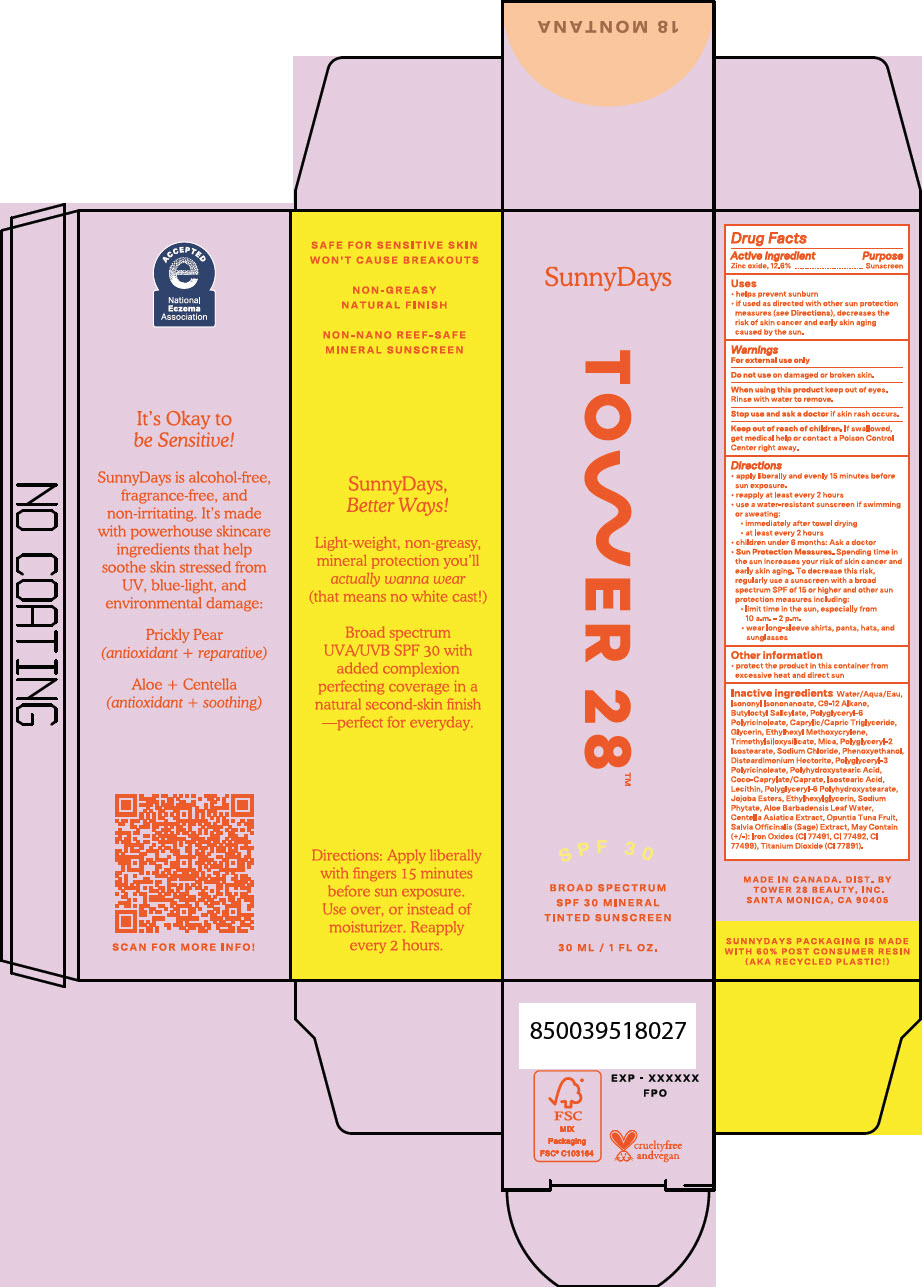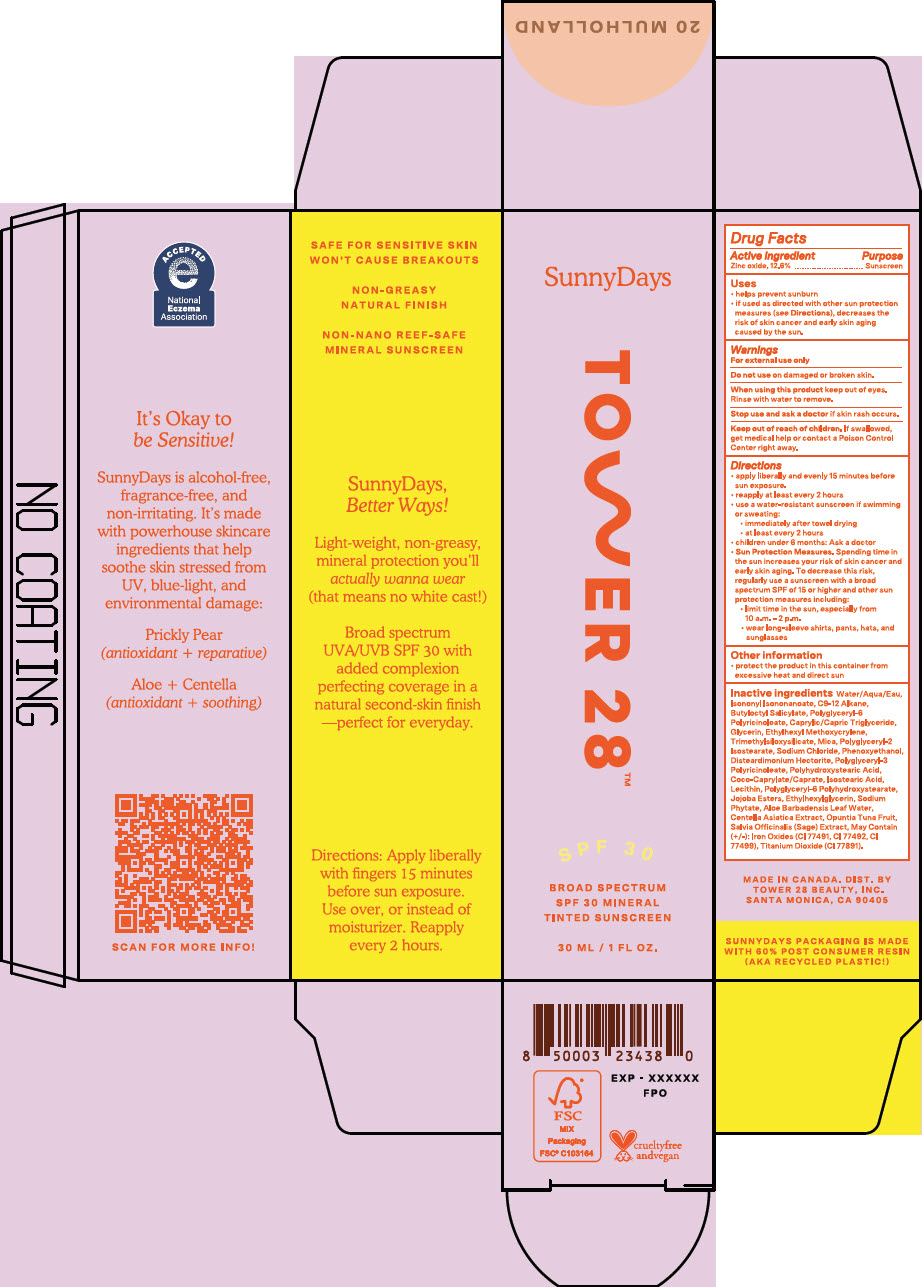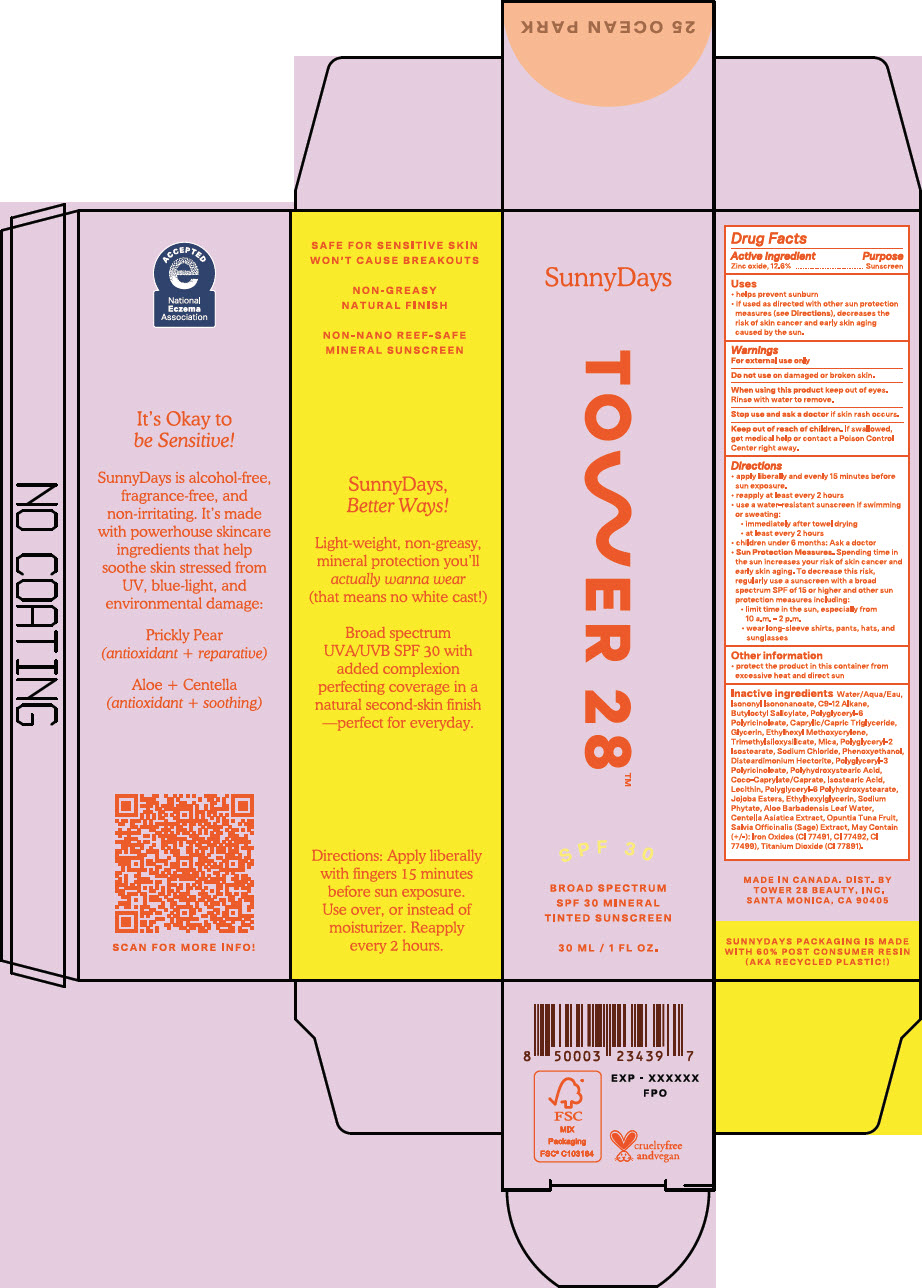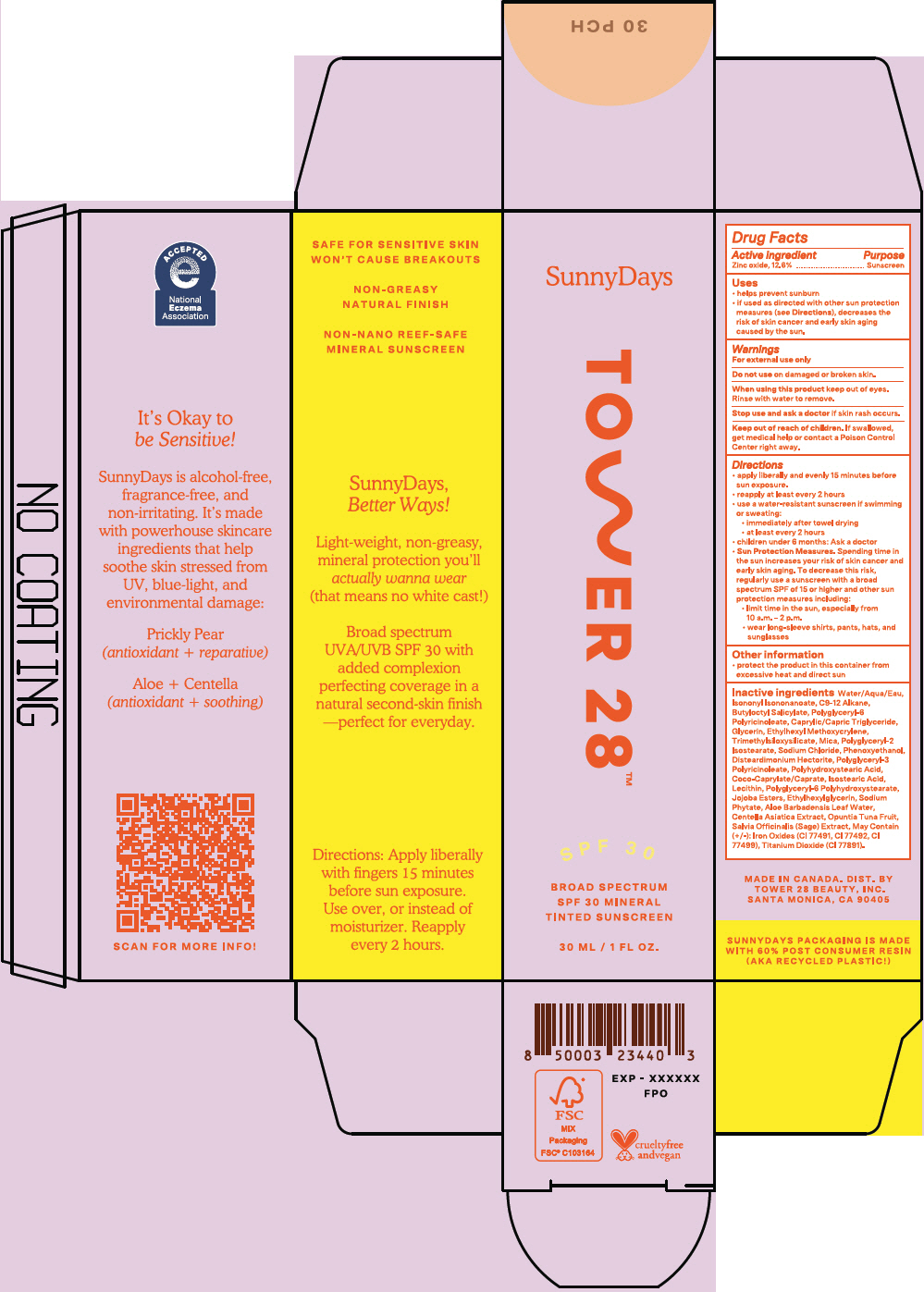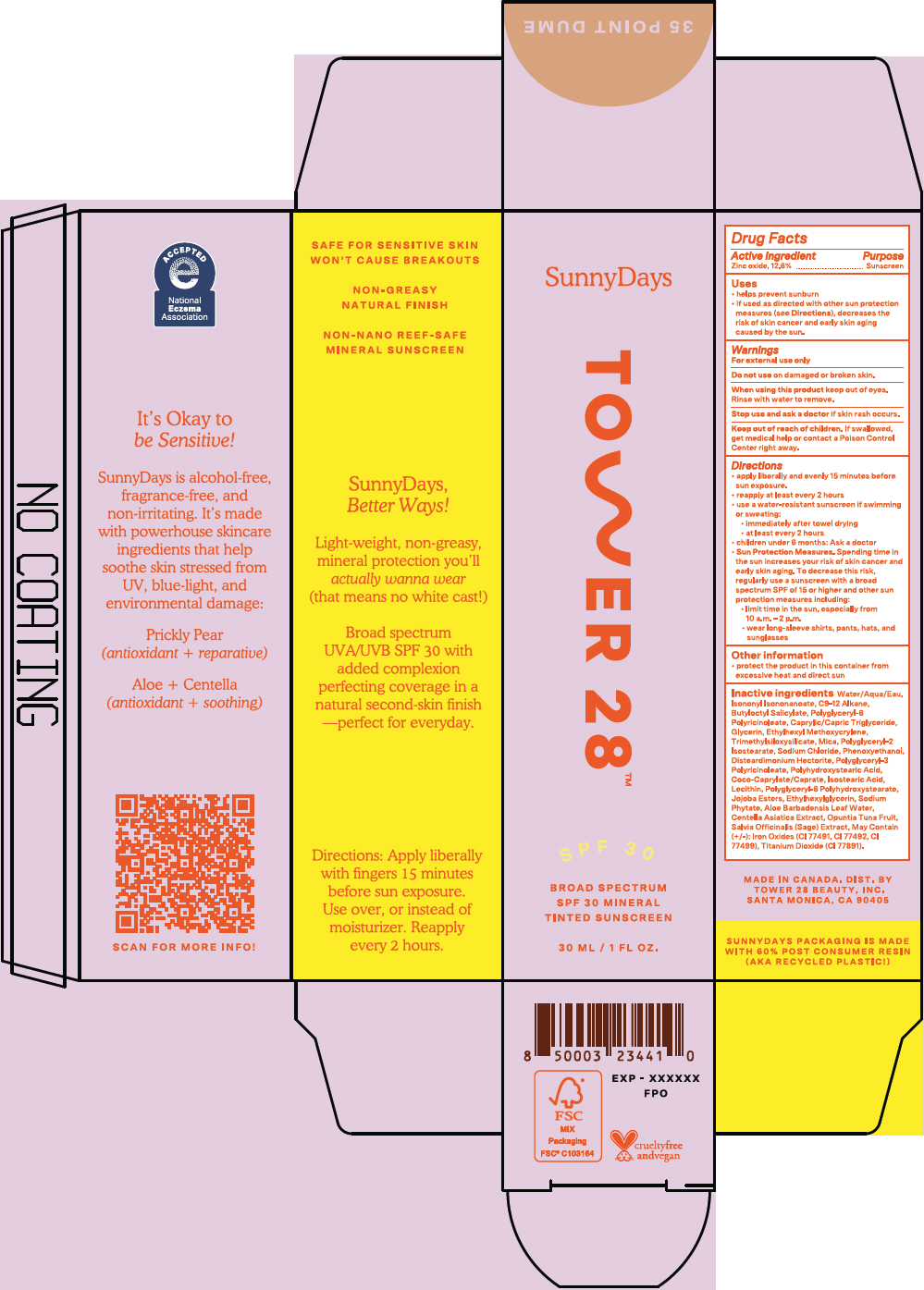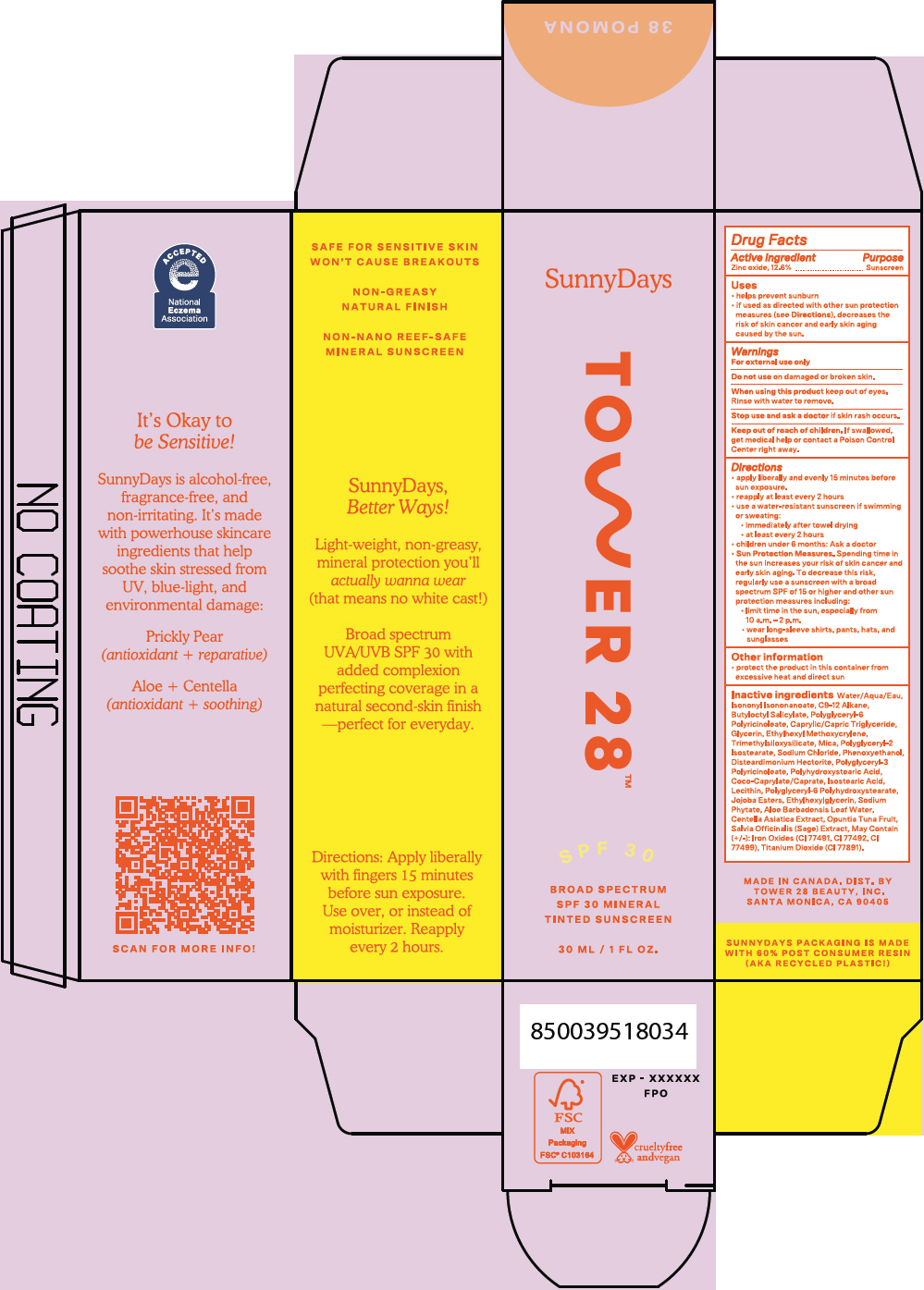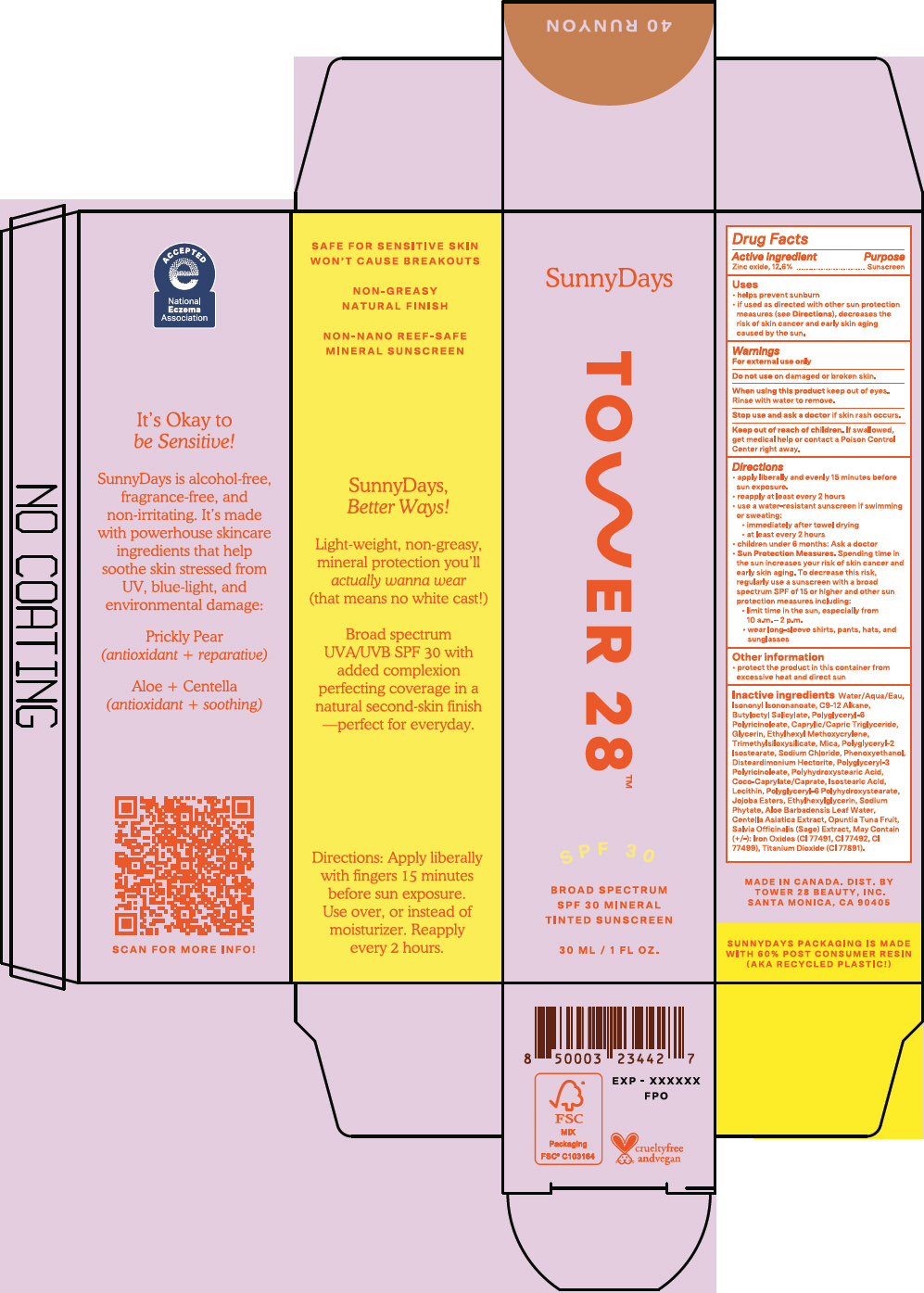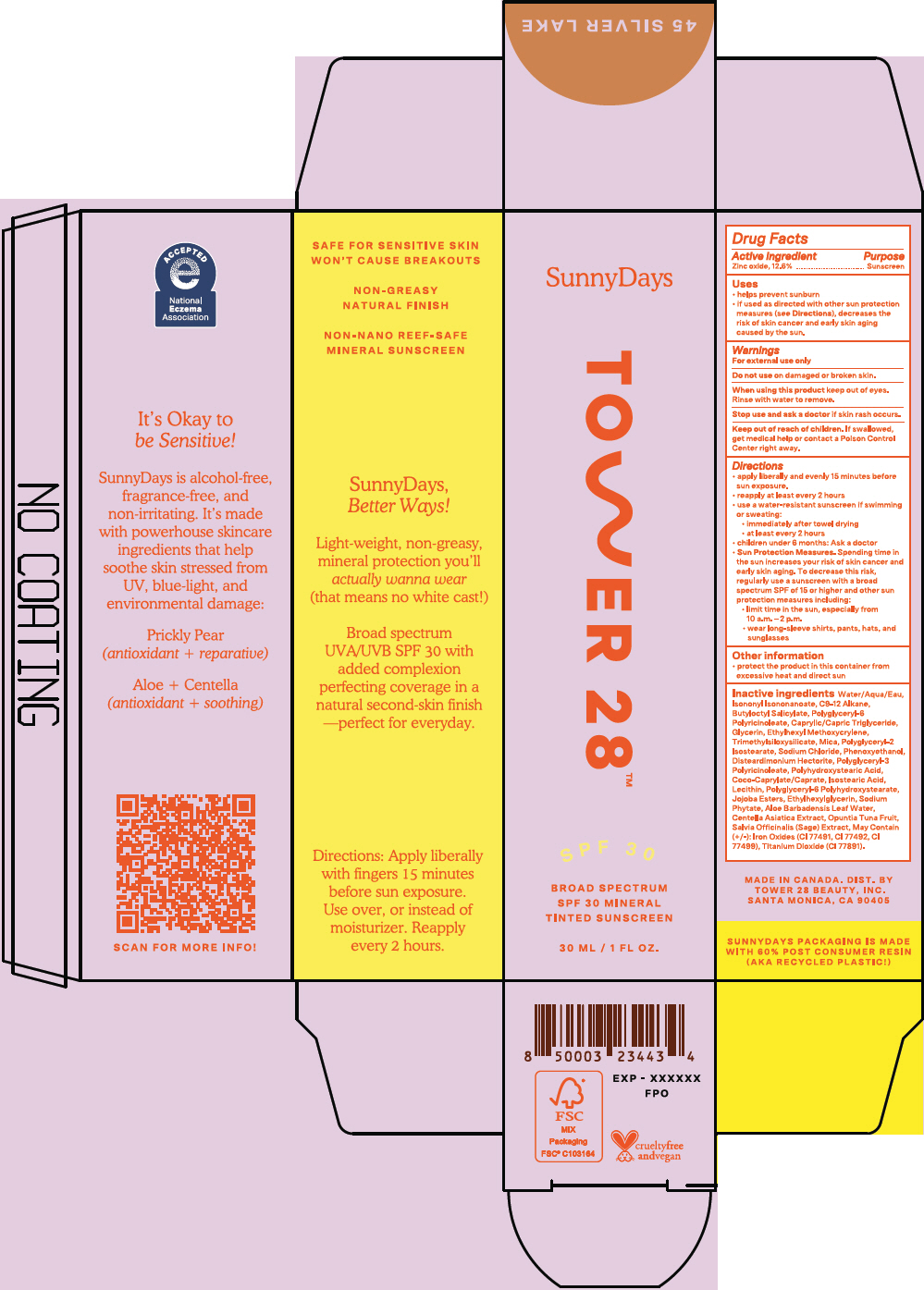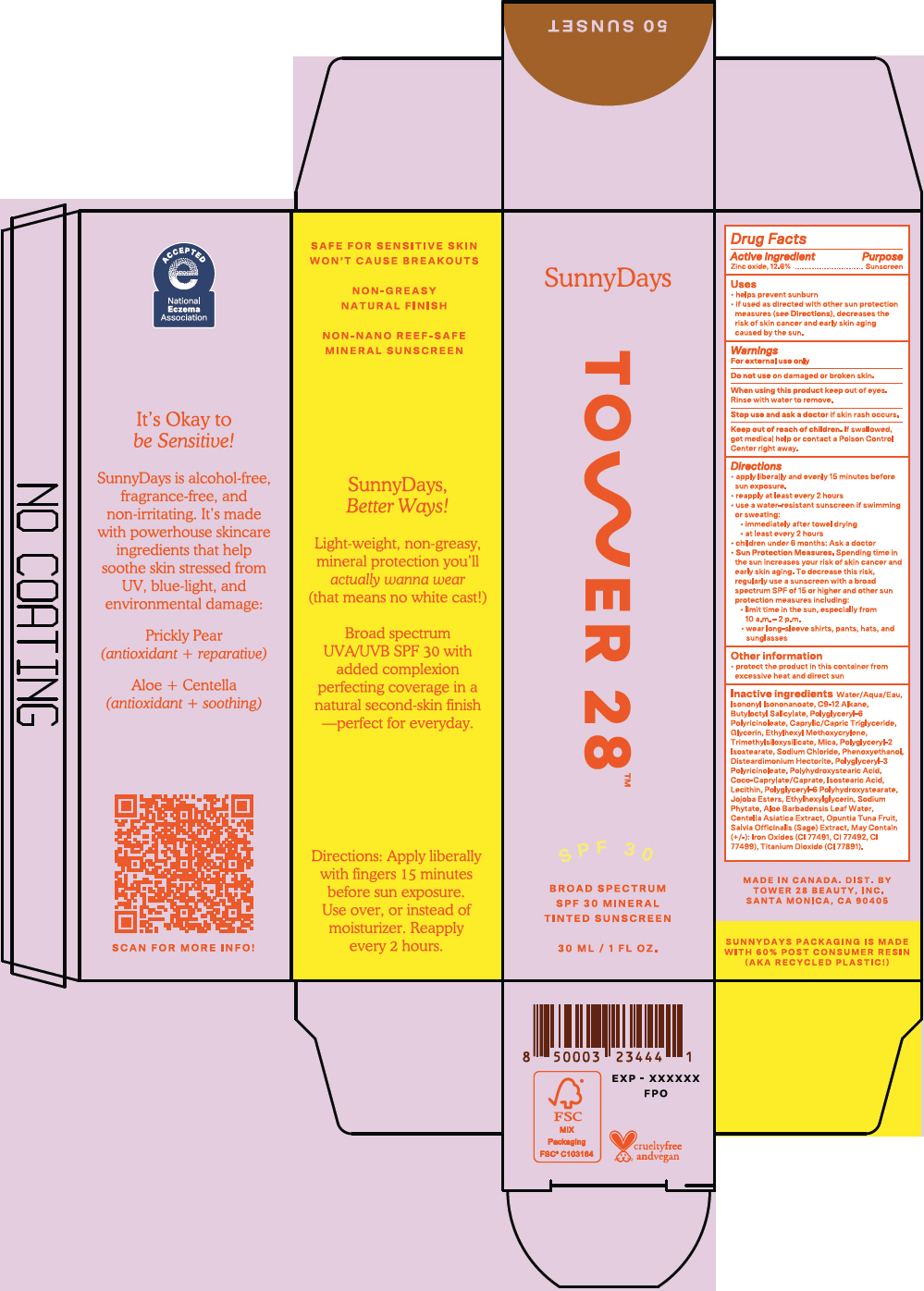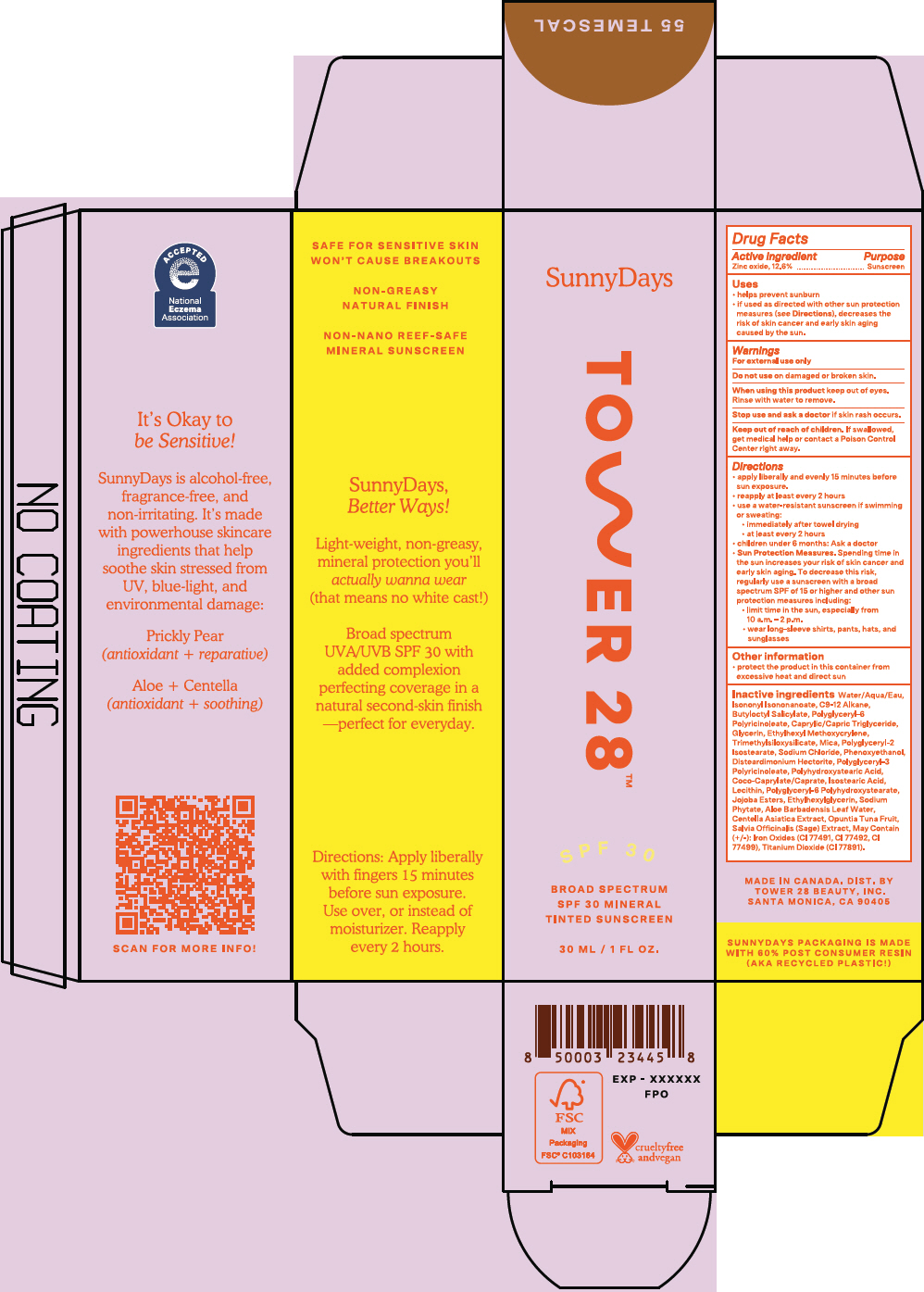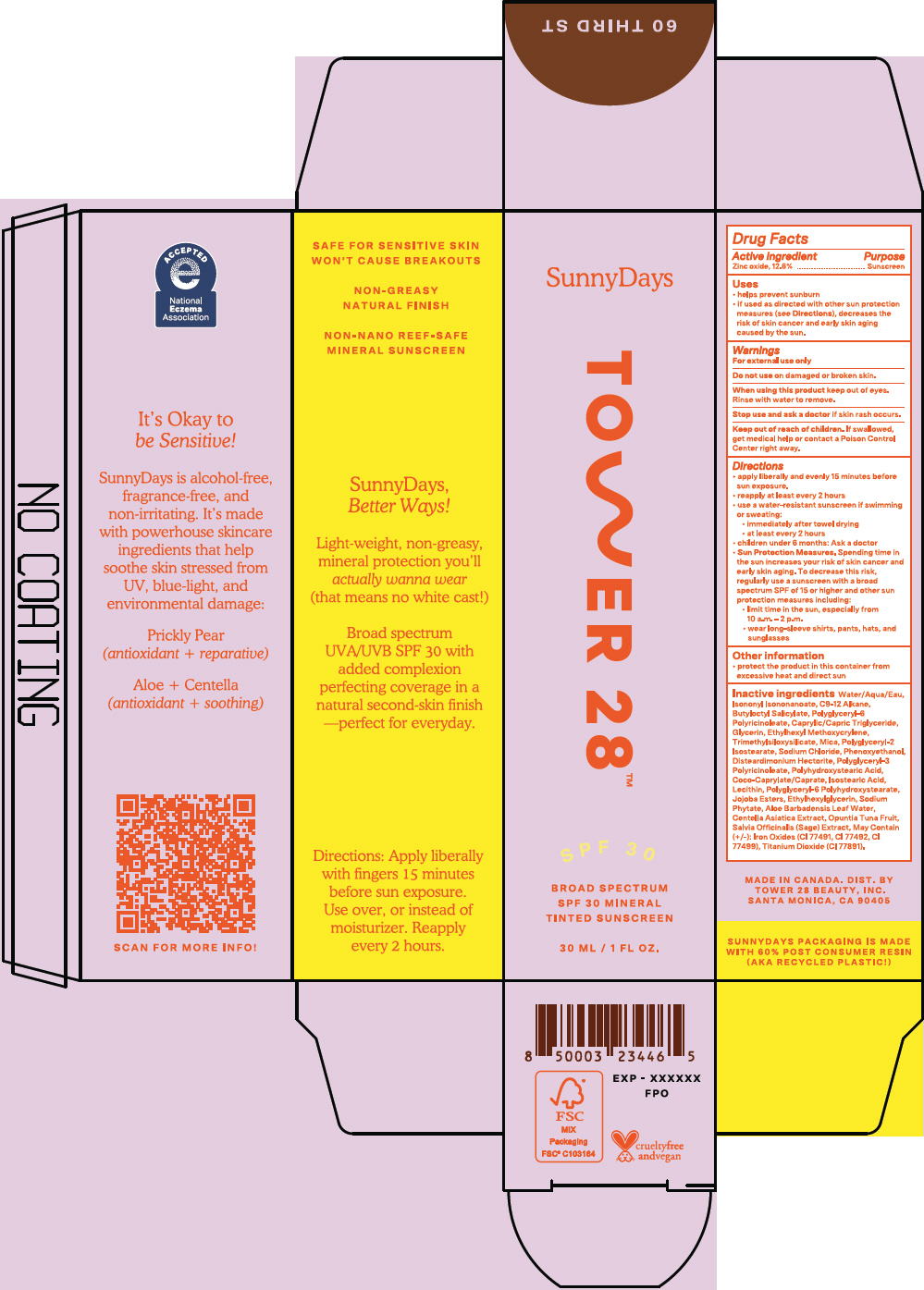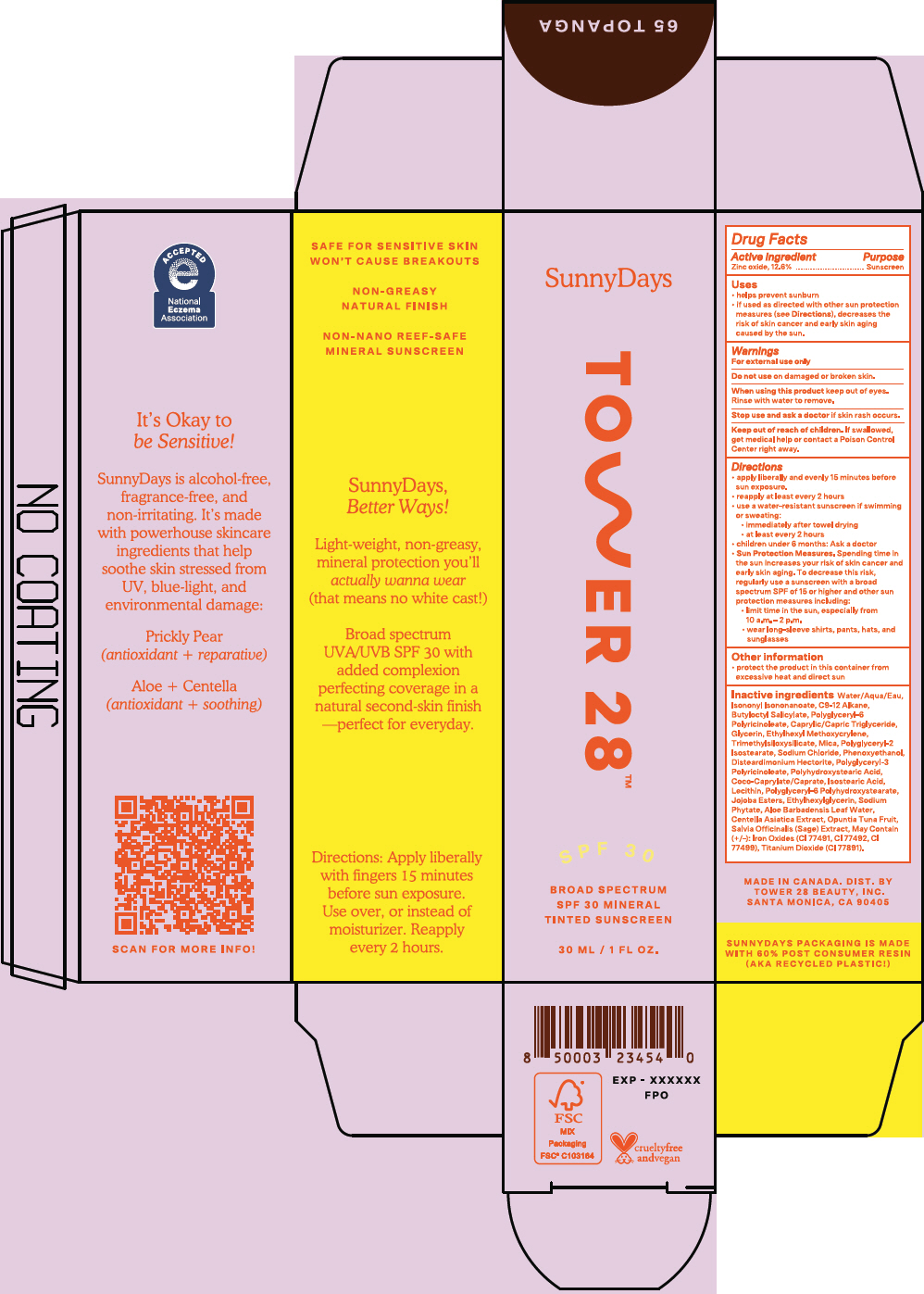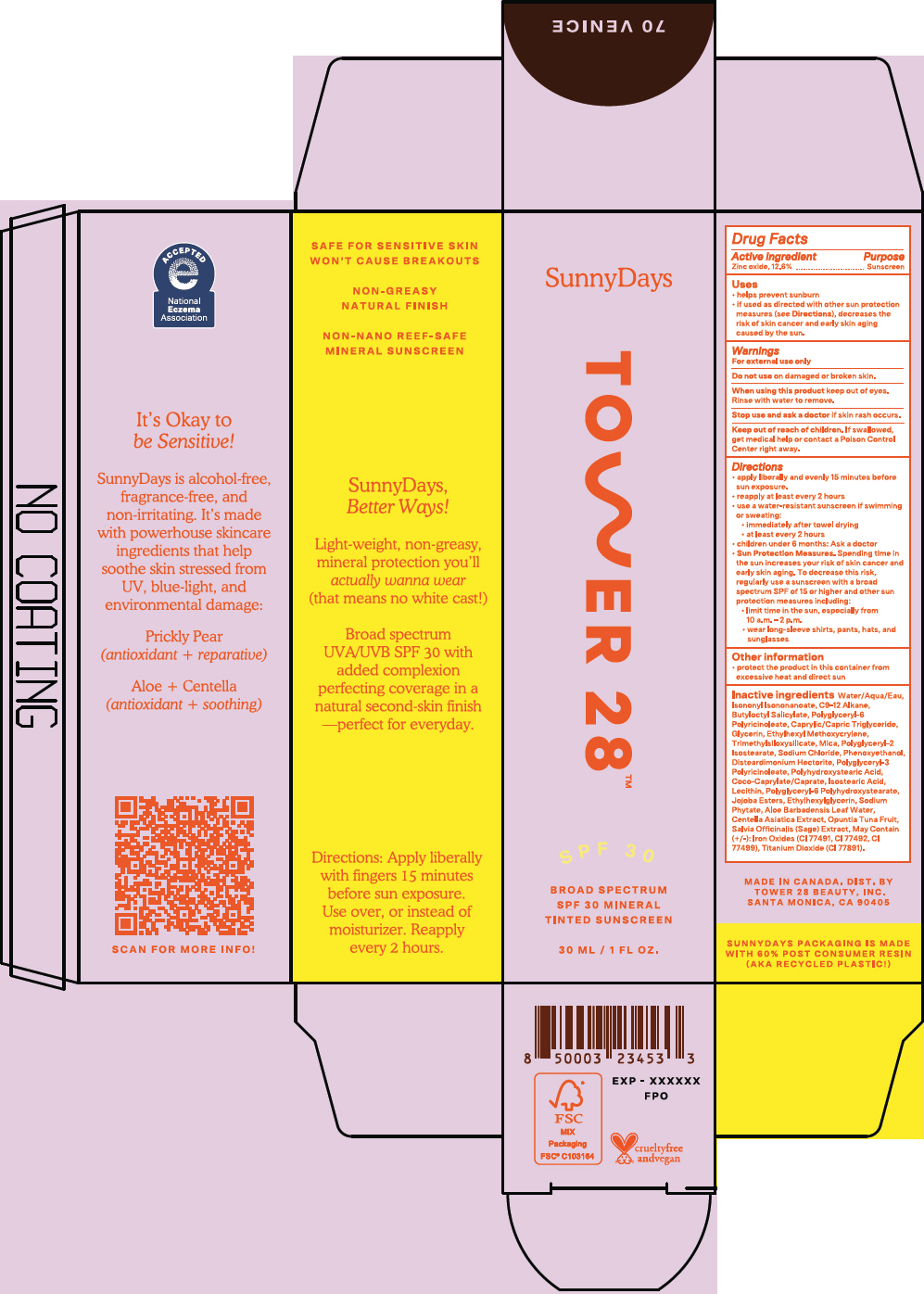 DRUG LABEL: SunnyDays Broad Spectrum SPF 30 Tinted Sunscreen 
NDC: 81899-005 | Form: LOTION
Manufacturer: Tower 28
Category: otc | Type: HUMAN OTC DRUG LABEL
Date: 20241016

ACTIVE INGREDIENTS: Zinc Oxide 126 mg/1 mL
INACTIVE INGREDIENTS: WATER; Isononyl Isononanoate; Butyloctyl Salicylate; Polyglyceryl-6 Polyricinoleate; MEDIUM-CHAIN TRIGLYCERIDES; Glycerin; Ethylhexyl Methoxycrylene; TRIMETHYLSILOXYSILICATE (M/Q 0.6-0.8); Mica; Polyglyceryl-2 Isostearate; Sodium Chloride; Phenoxyethanol; Disteardimonium Hectorite; POLYGLYCERYL-3 PENTARICINOLEATE; POLYHYDROXYSTEARIC ACID (2300 MW); COCOYL CAPRYLOCAPRATE; Isostearic Acid; EGG PHOSPHOLIPIDS; POLYGLYCERYL-2 DIPOLYHYDROXYSTEARATE; LECITHIN, SUNFLOWER; Ethylhexylglycerin; PHYTATE SODIUM; ALOE VERA LEAF; CENTELLA ASIATICA WHOLE; Opuntia Tuna Fruit; SALVIA OFFICINALIS ROOT; FERRIC OXIDE RED; FERRIC OXIDE YELLOW; FERROSOFERRIC OXIDE; TITANIUM DIOXIDE

SunnyDays Broad Spectrum SPF 30 Tinted Sunscreen

Drug Facts

Active ingredient

Zinc oxide, 12.6%

Purpose

Sunscreen

Uses

- helps prevent sunburn
- if used as directed with other sun protection measures (see Directions), decreases the risk of skin cancer and early skin aging caused by the sun.

Warnings

For external use only

Do not use on damaged or broken skin.

When using this product keep out of eyes. Rinse with water to remove.

Stop use and ask a doctor if skin rash occurs.

Keep out of reach of children. If swallowed, get medical help or contact a Poison Control Center right away.

Directions

- apply liberally and evenly 15 minutes before sun exposure.
- reapply at least every 2 hours
- use a water-resistant sunscreen if swimming or sweating:
  - immediately after towel drying
  - at least every 2 hours
- children under 6 months: Ask a doctor
- Sun Protection Measures. Spending time in the sun increases your risk of skin cancer and early skin aging. To decrease this risk, regularly use a sunscreen with a broad spectrum SPF of 15 or higher and other sun protection measures including:
  - limit time in the sun, especially from 10 a.m. – 2 p.m.
  - wear long-sleeve shirts, pants, hats, and sunglasses

Other information

- protect the product in this container from excessive heat and direct sun

Inactive ingredients

Water/Aqua/Eau, Isononyl Isononanoate, C9-12 Alkane, Butyloctyl Salicylate, Polyglyceryl-6 Polyricinoleate, Caprylic/Capric Triglyceride, Glycerin, Ethylhexyl Methoxycrylene, Trimethylsiloxysilicate, Mica, Polyglyceryl-2 Isostearate, Sodium Chloride, Phenoxyethanol, Disteardimonium Hectorite, Polyglyceryl-3 Polyricinoleate, Polyhydroxystearic Acid, Coco-Caprylate/Caprate, Isostearic Acid, Lecithin, Polyglyceryl-6 Polyhydroxystearate, Jojoba Esters, Ethylhexylglycerin, Sodium Phytate, Aloe Barbadensis Leaf Water, Centella Asiatica Extract, Opuntia Tuna Fruit, Salvia Officinalis (Sage) Extract, May Contain (+/-): Iron Oxides (CI 77491, CI 77492, CI 77499), Titanium Dioxide (CI 77891).

DIST. BY
TOWER 28 BEAUTY, INC.
SANTA MONICA, CA 90405

PRINCIPAL DISPLAY PANEL - 30 ML Tube Box - 5 Fairfax

SunnyDays

TOWER 28™

SPF 30

BROAD SPECTRUM
SPF 30 MINERAL
TINTED SUNSCREEN

30 ML / 1 FL OZ.

PRINCIPAL DISPLAY PANEL - 30 ML Tube Box - 10 Larchmont

SunnyDays

TOWER 28™

SPF 30

BROAD SPECTRUM
SPF 30 MINERAL
TINTED SUNSCREEN

30 ML / 1 FL OZ.

PRINCIPAL DISPLAY PANEL - 30 ML Tube Box - 13 La Cienega

SunnyDays

TOWER 28™

SPF 30

BROAD SPECTRUM
SPF 30 MINERAL
TINTED SUNSCREEN

30 ML / 1 FL OZ.

PRINCIPAL DISPLAY PANEL - 30 ML Tube Box - 15 Melrose

SunnyDays

TOWER 28™

SPF 30

BROAD SPECTRUM
SPF 30 MINERAL
TINTED SUNSCREEN

30 ML / 1 FL OZ.

PRINCIPAL DISPLAY PANEL - 30 ML Tube Box - 18 Montana

SunnyDays

TOWER 28™

SPF 30

BROAD SPECTRUM
SPF 30 MINERAL
TINTED SUNSCREEN

30 ML / 1 FL OZ.

PRINCIPAL DISPLAY PANEL - 30 ML Tube Box - 20 Mulholland

SunnyDays

TOWER 28™

SPF 30

BROAD SPECTRUM
SPF 30 MINERAL
TINTED SUNSCREEN

30 ML / 1 FL OZ.

PRINCIPAL DISPLAY PANEL - 30 ML Tube Box - 25 Ocean Park

SunnyDays

TOWER 28™

SPF 30

BROAD SPECTRUM
SPF 30 MINERAL
TINTED SUNSCREEN

30 ML / 1 FL OZ.

PRINCIPAL DISPLAY PANEL - 30 ML Tube Box - 30 PCH

SunnyDays

TOWER 28™

SPF 30

BROAD SPECTRUM
SPF 30 MINERAL
TINTED SUNSCREEN

30 ML / 1 FL OZ.

PRINCIPAL DISPLAY PANEL - 30 ML Tube Box - 35 Point Dume

SunnyDays

TOWER 28™

SPF 30

BROAD SPECTRUM
SPF 30 MINERAL
TINTED SUNSCREEN

30 ML / 1 FL OZ.

PRINCIPAL DISPLAY PANEL - 30 ML Tube Box - 38 Pomona

SunnyDays

TOWER 28™

SPF 30

BROAD SPECTRUM
SPF 30 MINERAL
TINTED SUNSCREEN

30 ML / 1 FL OZ.

PRINCIPAL DISPLAY PANEL - 30 ML Tube Box - 40 Runyon

SunnyDays

TOWER 28™

SPF 30

BROAD SPECTRUM
SPF 30 MINERAL
TINTED SUNSCREEN

30 ML / 1 FL OZ.

PRINCIPAL DISPLAY PANEL - 30 ML Tube Box - 45 Silver Lake

SunnyDays

TOWER 28™

SPF 30

BROAD SPECTRUM
SPF 30 MINERAL
TINTED SUNSCREEN

30 ML / 1 FL OZ.

PRINCIPAL DISPLAY PANEL - 30 ML Tube Box - 50 Sunset

SunnyDays

TOWER 28™

SPF 30

BROAD SPECTRUM
SPF 30 MINERAL
TINTED SUNSCREEN

30 ML / 1 FL OZ.

PRINCIPAL DISPLAY PANEL - 30 ML Tube Box - 55 Temescal

SunnyDays

TOWER 28™

SPF 30

BROAD SPECTRUM
SPF 30 MINERAL
TINTED SUNSCREEN

30 ML / 1 FL OZ.

PRINCIPAL DISPLAY PANEL - 30 ML Tube Box - 60 Third St

SunnyDays

TOWER 28™

SPF 30

BROAD SPECTRUM
SPF 30 MINERAL
TINTED SUNSCREEN

30 ML / 1 FL OZ.

PRINCIPAL DISPLAY PANEL - 30 ML Tube Box - 65 Topanga

SunnyDays

TOWER 28™

SPF 30

BROAD SPECTRUM
SPF 30 MINERAL
TINTED SUNSCREEN

30 ML / 1 FL OZ.

PRINCIPAL DISPLAY PANEL - 30 ML Tube Box - 70 Venice

SunnyDays

TOWER 28™

SPF 30

BROAD SPECTRUM
SPF 30 MINERAL
TINTED SUNSCREEN

30 ML / 1 FL OZ.